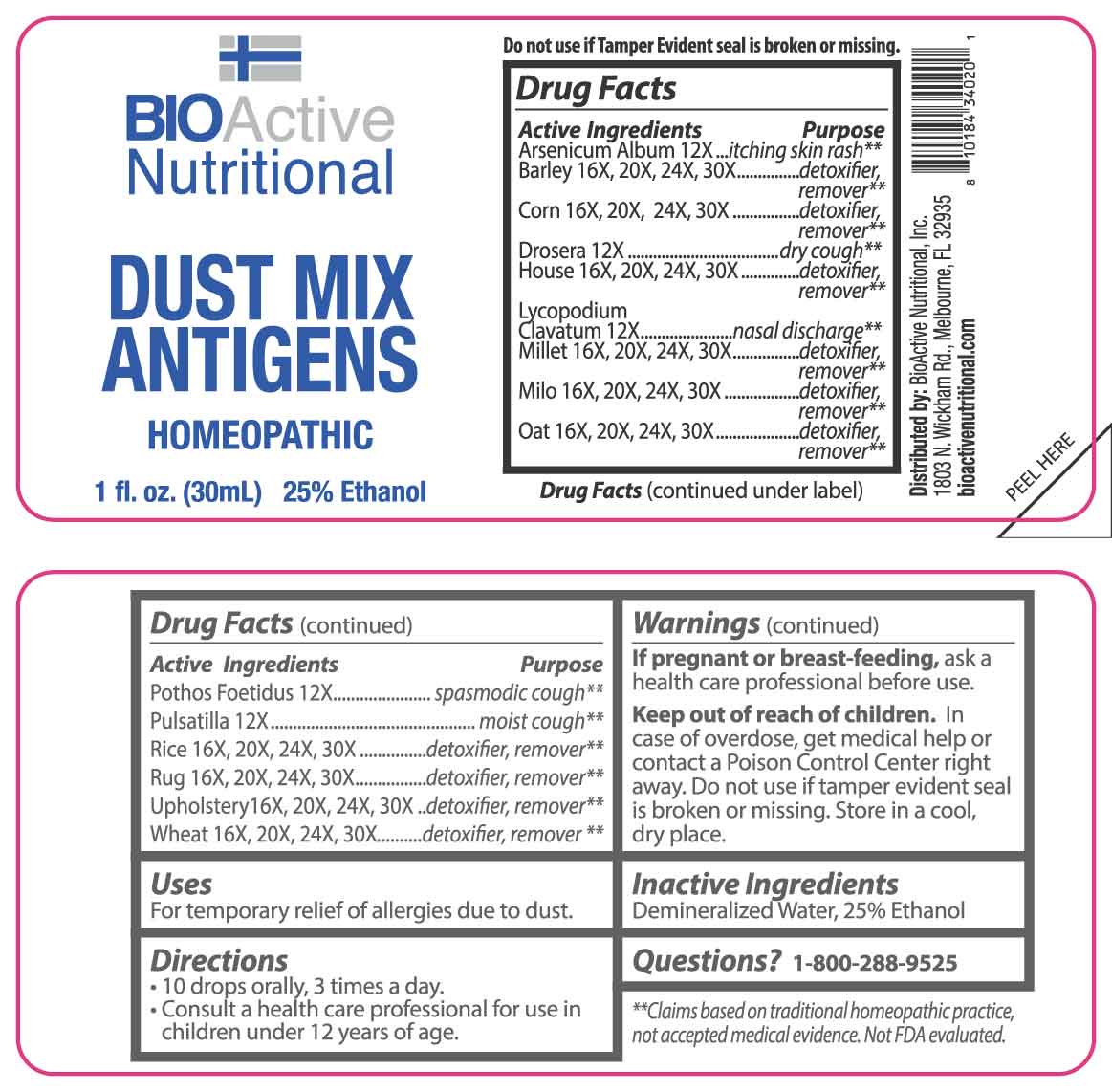 DRUG LABEL: Dust Mix Antigens
NDC: 43857-0624 | Form: LIQUID
Manufacturer: BioActive Nutritional, Inc.
Category: homeopathic | Type: HUMAN OTC DRUG LABEL
Date: 20250403

ACTIVE INGREDIENTS: ARSENIC TRIOXIDE 12 [hp_X]/1 mL; DROSERA ROTUNDIFOLIA WHOLE 12 [hp_X]/1 mL; LYCOPODIUM CLAVATUM SPORE 12 [hp_X]/1 mL; SYMPLOCARPUS FOETIDUS ROOT 12 [hp_X]/1 mL; PULSATILLA PRATENSIS WHOLE 12 [hp_X]/1 mL; BARLEY 16 [hp_X]/1 mL; CORN 16 [hp_X]/1 mL; HOUSE DUST 16 [hp_X]/1 mL; MILLET 16 [hp_X]/1 mL; SORGHUM BICOLOR WHOLE 16 [hp_X]/1 mL; OAT 16 [hp_X]/1 mL; WHITE RICE 16 [hp_X]/1 mL; WHEAT 16 [hp_X]/1 mL
INACTIVE INGREDIENTS: WATER; ALCOHOL

DRUG FACTS:

ACTIVE INGREDIENTS:

Arsenicum Album 12X, Barley 16X, 20X, 24X, 30X, Corn 16X, 20X, 24X, 30X, Drosera 12X, House 16X, 20X, 24X, 30X, Lycopodium Clavatum 12X, Millet 16X, 20X, 24X, 30X, Milo 16X, 20X, 24X, 30X, Oat 16X, 20X, 24X, 30X, Pothos Foetidus 12X, Pulsatilla 12X, Rice 16X, 20X, 24X, 30X, Rug 16X, 20X, 24X, 30X, Upholstery 16X, 20X, 24X, 30X, Wheat 16X, 20X, 24X, 30X.

PURPOSE:

Arsenicum Album – itching skin rash,** Barley – detoxifier remover,** Corn – detoxifier remover,** Drosera – dry cough,** House - detoxifier remover,** Lycopodium Clavatum – nasal discharge,** Millet - detoxifier remover,** Milo - detoxifier remover,** Oat - detoxifier remover,** Pothos Foetidus – spasmodic cough,** Pulsatilla – moist cough,** Rice - detoxifier remover,** Rug - detoxifier remover,** Upholstery - detoxifier remover,** Wheat - detoxifier remover**
**Claims based on traditional homeopathic practice, not accepted medical evidence. Not FDA Evaluated.

USES:

For temporary relief of allergies due to dust.

WARNINGS:

If pregnant or breast-feeding, ask a health care professional before use.

Keep out of reach of children. In case of overdose, get medical help or contact a Poison Control Center right away.

Do not use if tamper evident seal is broken or missing.

Store in a cool, dry place.

KEEP OUT OF REACH OF CHILDREN:

In case of overdose, get medical help or contact a Poison Control Center right away.

DIRECTIONS:

• 10 drops orally, 3 times a day.

• Consult a health care professional for use in children under 12 years of age.

INACTIVE INGREDIENTS:

Demineralized Water, 25% Ethanol

QUESTIONS:

Distributed by:
BioActive Nutritional, Inc.
1803 N. Wickham Rd.
Melbourne, FL 32935
bioactivenutritional.com

1-800-288-9525

PACKAGE LABEL DISPLAY:

BIOActive Nutritional

DUST MIX

ANTIGENS

HOMEOPATHIC

1 FL OZ (30 ml)